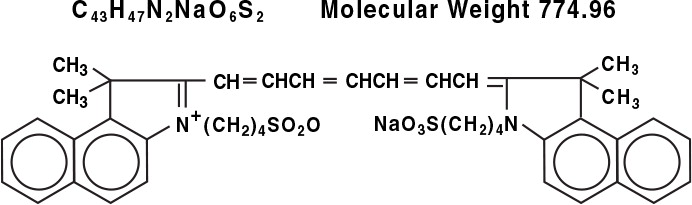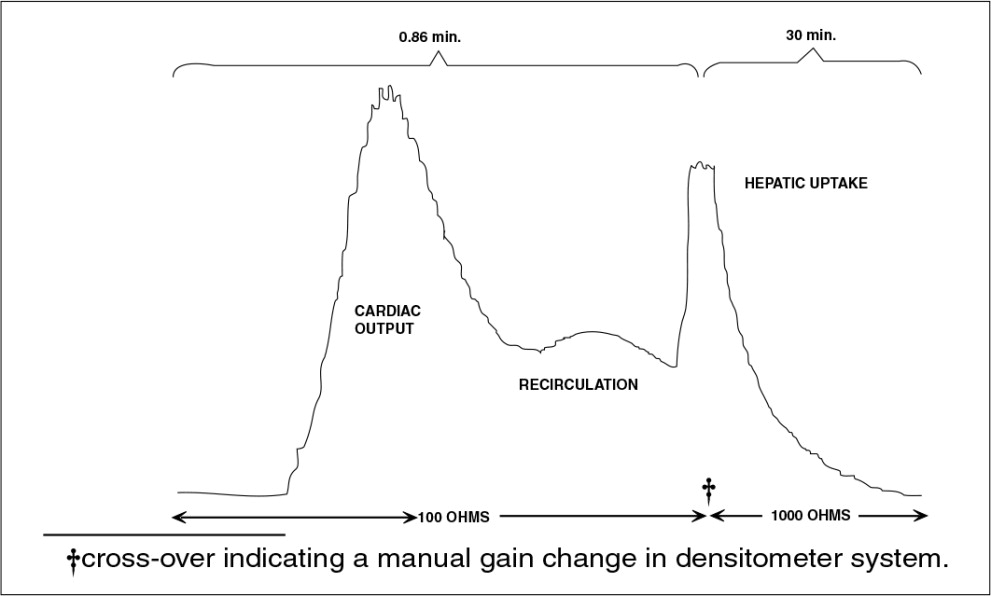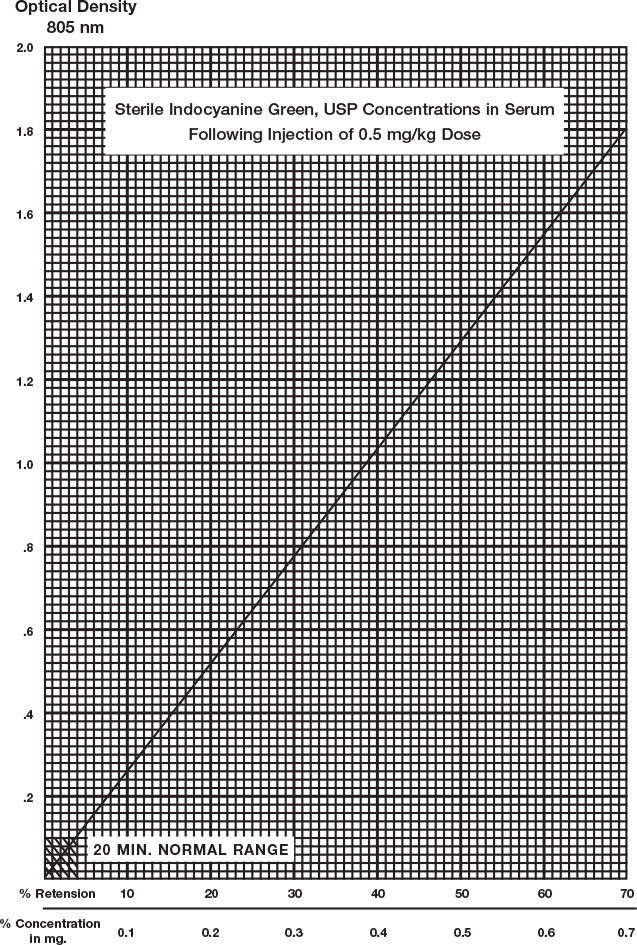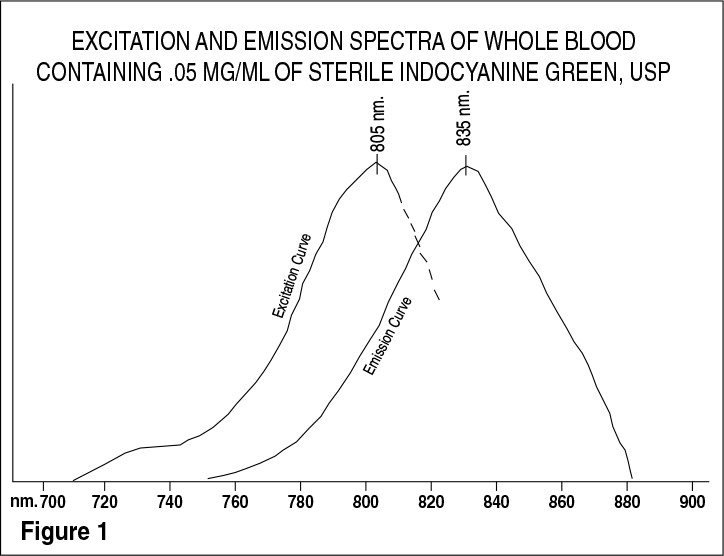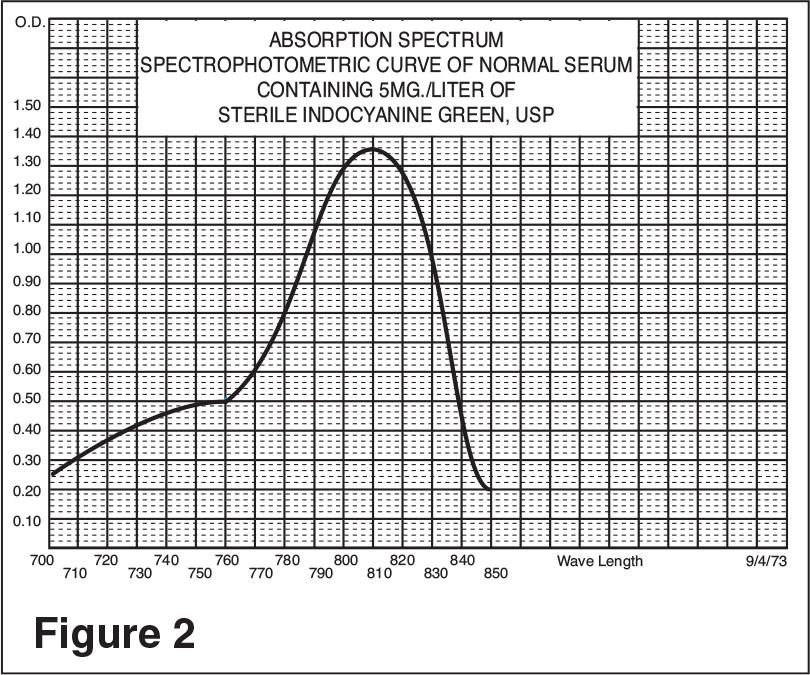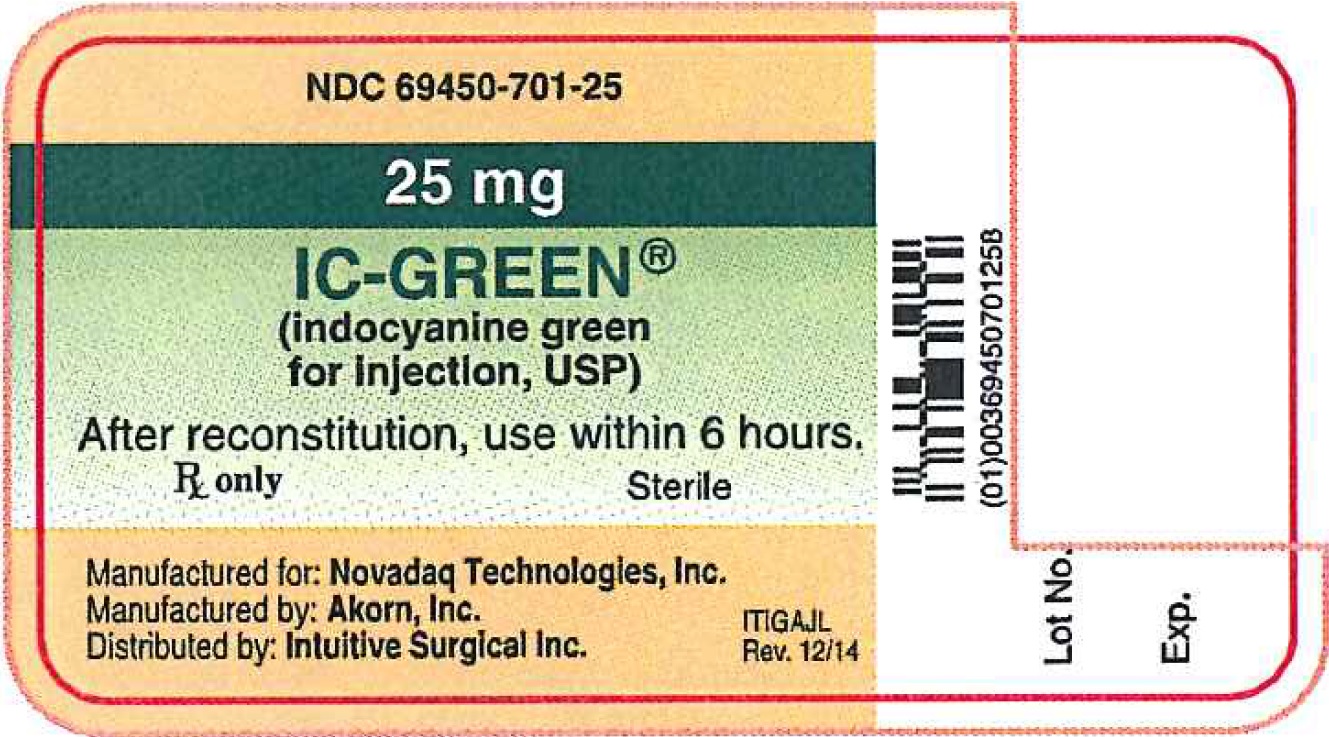 DRUG LABEL: IC-GREEN
NDC: 69450-701 | Form: INJECTION, POWDER, LYOPHILIZED, FOR SOLUTION
Manufacturer: Novadaq Technologies, Inc.
Category: prescription | Type: HUMAN PRESCRIPTION DRUG LABEL
Date: 20150302

ACTIVE INGREDIENTS: Indocyanine green 25 mg/1 1

IC-GREEN™

(indocyanine green for injection, USP)

Sterile
Rx only

DESCRIPTION

IC‑GREEN™ is a sterile, lyophilized green powder containing 25 mg of indocyanine green with no more than 5% sodium iodide. It is packaged with Aqueous Solvent consisting of Sterile Water for Injection used to dissolve the indocyanine green. IC‑GREEN™ is to be administered intravenously.

Indocyanine green is a water soluble, tricarbocyanine dye with a peak spectral absorption at 800 nm. The chemical name for Indocyanine Green is 1 H‑Benz[e]indolium, 2‑[7‑[1,3‑dihydro‑1,1‑dimethyl‑3‑(4‑sulfobutyl)‑2H‑benz[e]indol‑2‑ylidene]‑1,3,5-heptatrienyl]‑1,1‑dimethyl‑3‑(4‑sulfobutyl)‑,hydroxide, inner salt, sodium salt. IC‑GREEN™ has a pH of approximately 6.5 when reconstituted. Each vial of IC‑GREEN™ contains 25 mg of indocyanine green as a sterile lyophilized powder.

CLINICAL PHARMACOLOGY

Following intravenous injection, IC‑GREEN™ is rapidly bound to plasma protein, of which albumin is the principle carrier (95%). IC‑GREEN™ undergoes no significant extrahepatic or enterohepatic circulation; simultaneous arterial and venous blood estimations have shown negligible renal, peripheral, lung or cerebro‑spinal uptake of the dye. IC‑GREEN™ is taken up from the plasma almost exclusively by the hepatic parenchymal cells and is secreted entirely into the bile. After biliary obstruction, the dye appears in the hepatic lymph, independently of the bile, suggesting that the biliary mucosa is sufficiently intact to prevent diffusion of the dye, though allowing diffusion of bilirubin. These characteristics make IC‑GREEN™ a helpful index of hepatic function.

The plasma fractional disappearance rate at the recommended 0.5 mg/kg dose has been reported to be significantly greater in women than in men, although there was no significant difference in the calculated value for clearance.

INDICATIONS AND USAGE

For determining cardiac output, hepatic function and liver blood flow, and for ophthalmic angiography.

CONTRAINDICATIONS

IC‑GREEN™ contains sodium iodide and should be used with caution in patients who have a history of allergy to iodides.

WARNINGS

Anaphylactic deaths have been reported following IC‑GREEN™ administration during cardiac catheterization.

PRECAUTIONS

GENERAL PRECAUTIONS

General: IC‑GREEN™ Powder and Solution: IC‑GREEN™ is unstable in aqueous solution and must be used within 6 hours. However, the dye is stable in plasma and whole blood so that samples obtained in discontinuous sampling techniques may be read hours later. Sterile techniques should be used in handling the dye solution as well as in the performance of the dilution curves.

IC‑GREEN™ (indocyanine green for injection) powder may cling to the vial or lump together because it is freeze‑dried in the vials.

DRUG INTERACTIONS

Drug Interactions: Heparin preparations containing sodium bisulfite reduce the absorption peak of IC‑GREEN™ in blood and, therefore, should not be used as an anticoagulant for the collection of samples for analysis.

LABORATORY TESTS

Drug/Laboratory Test Interactions: Radioactive iodine uptake studies should not be performed for at least a week following the use of IC‑GREEN™.

CARCINOGENESIS AND MUTAGENESIS AND IMPAIRMENT OF FERTILITY

Carcinogenesis, Mutagenesis, Impairment of Fertility: No studies have been performed to evaluate the carcinogenicity, mutagenicity, or impairment of fertility.

PREGNANCY

Pregnancy: Teratogenic Effects: Pregnanacy Category C: Animal Reproduction studies have not been conducted with IC‑GREEN™. It is also not known whether IC‑GREEN™ can cause fetal harm when administered to a pregnant woman or can affect reproduction capacity. IC‑GREEN™ should be given to a pregnant woman only if clearly indicated.

NURSING MOTHERS

Nursing Mothers: It is not known whether this drug is excreted in human milk. Because many drugs are excreted in human milk, caution should be exercised when IC‑GREEN™ is administered to a nursing woman.

PEDIATRIC USE

Pediatric Use: Safety and effectiveness in pediatric patients have been established.

GERIATRIC USE

Geriatric Use: No overall differences in safety or effectiveness have been observed between elderly and younger patients.

ADVERSE REACTIONS

Anaphylactic or urticarial reactions have been reported in patients with or without history of allergy to iodides. If such reactions occur, treatment with the appropriate agents, e.g., epinephrine, antihistamines, and corticosteroids should be administered.

OVERDOSAGE

There are no data available describing the signs, symptoms, or laboratory findings accompanying overdosage. The LD50 after I.V. administration ranges between 60 and 80 mg/kg in mice, 50 and 70 mg/kg in rats and 50 and 80 mg/kg in rabbits.

DOSAGE AND ADMINISTRATION

INDICATOR‑DILUTION STUDIES: IC‑GREEN™ permits recording of the indicator‑dilution curves for both diagnostic and research purpose independently of fluctuations in oxygen saturation. In the performance of dye dilution curves, a known amount of dye is usually injected as a single bolus as rapidly as possible via a cardiac catheter into selected sites in the vascular system. A recording instrument (oximeter or densitometer) is attached to a needle or catheter for sampling of the dye‑blood mixture from a systemic arterial sampling site.

Under sterile conditions, the IC‑GREEN™ powder should be dissolved with the Aqueous Solvent provided for this product, and the solution used within 6 hours after it is prepared. If a precipitate is present, discard the solution. The amount of solvent to be used can be calculated from the dosage form which follows. It is recommended that the syringe used for injection of the dye be rinsed with this diluent. Isotonic saline should be used to flush the residual dye from the cardiac catheter into the circulation so as to avoid hemolysis. With the exception of the rinsing of the dye injection syringe, saline is used in all other parts of the catheterization procedure.

This matter of rinsing the dye syringe with distilled water may not be critical, since it is known that an amount of sodium chloride sufficient to make an isotonic solution may be added to dye that has first been dissolved in distilled water. This procedure has been used for constant‑rate injection techniques without precipitation of the dye.

The usual doses of IC‑GREEN™ which have been used for dilution curves are as follows:

 | Adults ‑ | 5.0 mg
 | Children ‑ | 2.5 mg
 | Infants ‑ | 1.25 mg

These doses of the dye are usually injected in a mL volume. An average of five dilution curves are required in the performance of a diagnostic cardiac catheterization. The total dose of dye injected should be kept below 2 mg/kg.

Calibrating Dye Curves: To quantitate the dilution curves, standard dilutions of IC‑GREEN™ in whole blood are made as follows. It is strongly recommended that the same dye that was used for the injections be used in the preparation of these standard dilutions. The most concentrated dye solution is made by accurately diluting 1 mL of the 5 mg/mL dye with 7 mL of distilled water. This concentration is then successively halved by diluting 4 mL of the previous concentration with 4 mL of distilled water. (If a 2.5 mg/mL concentration was used for the dilution curves, 1 mL of the 2.5 mg/mL dye is added to 3 mL of distilled water to make the most concentrated "standard" solution. This concentration is then successively halved by diluting 2 mL of the previous concentration with 2 mL of distilled water.) Then 0.2 mL portions (accurately measured from a calibrated syringe) of these dye solutions are added to 5 mL aliquots of the subject's blood, giving final concentrations of the dye in blood beginning with 24.0 mg/liter, approximately (actual concentration depends on the exact volume of dye added). This concentration is, of course, successively halved in the succeeding aliquots of the subject's blood. These aliquots of blood containing known amounts of dye, as well as a blank sample of which 0.2 mL of saline containing no dye has been added, are then passed through the detecting instrument and a calibration curve is constructed from the deflections recorded.

HEPATIC FUNCTION STUDIES: Due to its absorption spectrum, changing concentrations of IC‑GREEN™ (indocyanine green for injection) in the blood can be monitored by ear densitometry or by obtaining blood specimens at timed intervals. The technique for both methods is as follows.

The patient should be studied in a fasting, basal state. The patient should be weighed and the dosage calculated on the basis of 0.5 mg/kg of body weight.

Under sterile conditions, the IC‑GREEN™ powder should be dissolved with the Aqueous Solvent provided. Exactly 5 mL of aqueous solvent should be added to the 25 mg vial giving 5 mg of dye per mL of solution.

Inject the correct amount of dye into the lumen of an arm vein as rapidly as possible, without allowing the dye to escape outside the vein. (If the photometric method is used, prior to injecting IC‑GREEN™, withdraw 6 mL of venous blood from the patient's arm for serum blank and standard curve construction, and through the same needle, inject the correct amount of dye.)

Ear Densitometry: Ear oximetry has also been used and makes it possible to monitor the appearance and disappearance of IC‑GREEN™ without the necessity of withdrawal and spectrophotometric analysis of blood samples for calibration. An ear densitometer which has a compensatory photo‑electric cell to correct for changes in blood volume and hematocrit, and a detection photocell which registers levels has been described. This device permits simultaneous measurement of cardiac output, blood volume and hepatic clearance of IC‑GREEN™* and was found to provide a reliable index of plasma removal kinetics after single injections or continuous intrusions of IC‑GREEN™. This technique was employed in newborn infants, healthy adults and in children and adults with liver disease. The normal subject has a removal rate of 18‑24% per minute. Due to the absence of extra‑hepatic removal, IC‑GREEN™ was found to be ideally suited for serial study of severe chronic liver disease and to provide a stable measurement of hepatic blood flow. In larger doses, IC‑GREEN™ has proven to be particularly valuable in detecting drug‑induced alterations of hepatic function and in the detection of mild liver injury.

Using the ear densitometer, a dosage of 0.5 mg/kg in normal subjects gives the following clearance pattern.

*Dichromatic earpiece densitometer supplied by The Waters Company, Rochester, Minnesota.

Photometric Method -

Determination Using Percentage Retention of Dye:

A typical curve obtained by plotting dye concentration versus optical density is shown opposite. Percent retention can be read from this plot.

If more accurate results are desired, a curve using the patient's blood and the vial of IC-GREEN™ being used in the determination can be constructed as follows:

1. Take 6 mL of non-dye-containing venous blood from the patient's arm. Place in a test tube and allow the blood to clot. The serum is separated by centrifugation.
2. Pipette 1 mL of the serum into a microcuvette.
3. Add 1 lambda (λ) of the 5 mg/mL aqueous IC‑GREEN™ (sterile indocyanine green) solution to the serum, giving a dilution of 5 mg/liter, the standard for 50% retention. (The addition of 2 lambda (λ) of the 5 mg/mL IC‑GREEN™ solution would give 100% retention; however, this concentration cannot be read on the spectrophotometer.)
4. The optical density of this solution is read at 805 nm, using normal serum as the blank.
5. Using graph paper similar to that used in the illustration, plot the 50% figure obtained in Step 4, and draw a line connecting this point with the zero coordinates.

Percentage Retention: A single 20‑minute sample (withdrawn from a vein in the opposite arm to that injected) is allowed to clot, centrifuged and its optical density is determined at 805 nm using the patient's normal serum as the blank. Dye concentration is read from the curve above. A single 20‑minute sample of serum in healthy subjects should contain no more than 4% of the initial concentration of the dye. The use of percentage retention is less accurate than percentage disappearance rate, but provides reproducible results. Hemolysis does not interfere with a reading.

Determination Using Disappearance Rate of Dye: To calculate the percentage disappearance rate, obtain samples at 5, 10, 15 and 20 minutes after injecting the dye. Prepare the sample as in the previous section and measure the optical densities at 805 nm, using the patient's normal serum as the blank. The IC‑GREEN™ concentration in each timed specimen can be determined by using the concentration curve illustrated. Plot values on semilogarithmic paper.

Specimens containing IC‑GREEN™ should be read at the same temperature since its optical density is influenced by temperature variations.

Normal Values: Percentage disappearance rate in healthy subjects is 18‑24% per minute. Normal biological half‑time is 2.5 ‑ 3.0 minutes.

OPHTHALMIC ANGIOGRAPHY STUDIES: The excitation and emission spectra (Figure 1) and the absorption spectra (Figure 2) of IC‑GREEN™ make it useful in ophthalmic angiography. The peak absorption and emission of IC‑GREEN™ lie in a region (800‑850 nm) where transmission of energy by the pigment epithelium is more efficient than in the region of visible light energy. IC‑GREEN™ also has the property of being nearly 98% bound to blood protein, and therefore, excessive dye extravasation does not take place in the highly fenestrated choroidal vasculature. It is, therefore, useful in both absorption and fluorescence infrared angiography of the choroidal vasculature when using appropriate filters and film in a fundus camera.

Dosages up to 40 mg IC‑GREEN™ dye in 2 mL of aqueous solvent have been found to give optimal angiograms, depending on the imaging equipment and technique used. The antecubital vein injected IC‑GREEN™ dye bolus should immediately be followed by a 5 mL bolus of normal saline.

Clinically, angiograms of uniformly good quality can be assured only after taking care to optimize the contributions of all possible factors such as, patient cooperation and dye injection. The foregoing injection regimen is designed to provide delivery of a spatially limited dye bolus of optimal concentration to the choroidal vasculature following intravenous injection.

HOW SUPPLIED:

IC‑GREEN™ is supplied in a kit (NDC 69450‑701‑02) containing six 25 mg IC‑GREEN™ vials and six 10 mL Aqueous Solvent ampules:

NDC 69450‑701‑25 IC‑GREEN™ vial. 25 mg fill in 20 mL vial.
NDC 17478‑701‑10 Aqueous Solvent ampule. 10 mL fill in 10 mL ampule.

STORAGE:

Store at 20˚ to 25˚C (68˚ to 77˚F) [see USP Controlled Room Temperature].

Rx only

Manufactured by: Akorn, Inc.
Lake Forest, IL 60045

Manufactured for: Novadaq Technologies Inc.
Richmond, BC, Canada, V6V 2A2

Distributed by: Intuitive Surgical Inc.
Sunnyvale, CA 94086

da Vinci. Surgery
ITIG00N
Rev. 12/14

Principal Display Panel - 25mg Vial Label

NDC 69450-701-25

25 mg

IC-GREEN®

(indocyanine green

For injection, USP)

After reconstitution, use within 6 hours.

Rx only Sterile

Manufactured for: | Novadaq Technologies, Inc.
Manufactured by: | Akorn, Inc.
Distributed by: | Intuitive Surgical Inc.